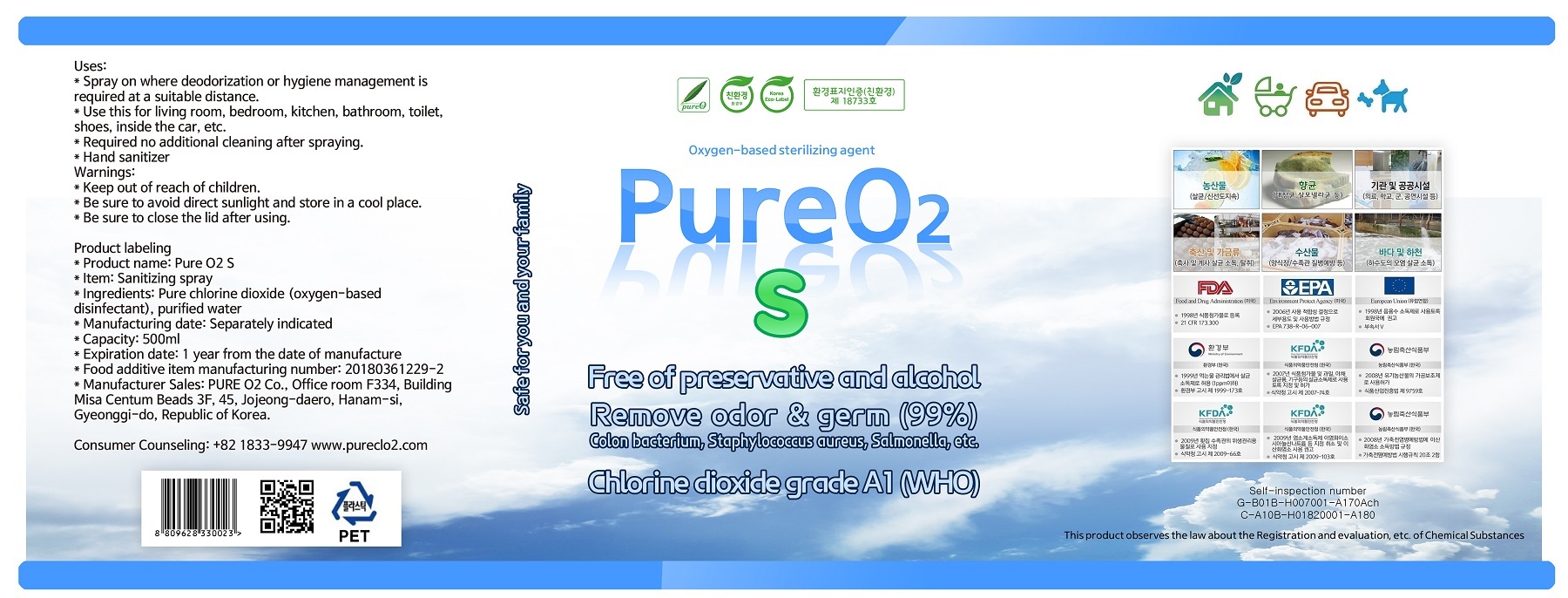 DRUG LABEL: PURE O2 S
NDC: 75124-0007 | Form: LIQUID
Manufacturer: Pure O2
Category: otc | Type: HUMAN OTC DRUG LABEL
Date: 20200501

ACTIVE INGREDIENTS: CHLORINE DIOXIDE 0.005 g/100 mL
INACTIVE INGREDIENTS: WATER

Drug Facts

ACTIVE INGREDIENT

chlorine dioxide

INACTIVE INGREDIENT

water

PURPOSE

remove odor and germ

KEEP OUT OF REACH OF THE CHILDREN

INDICATIONS AND USAGE

hand sanitizer

WARNINGS

■ For external use only.

■ Do not use in eyes.

■ lf swallowed, get medical help promptly.

■ Stop use, ask doctor lf irritation occurs.

■ Keep out of reach of children.

DOSAGE AND ADMINISTRATION

for external use only